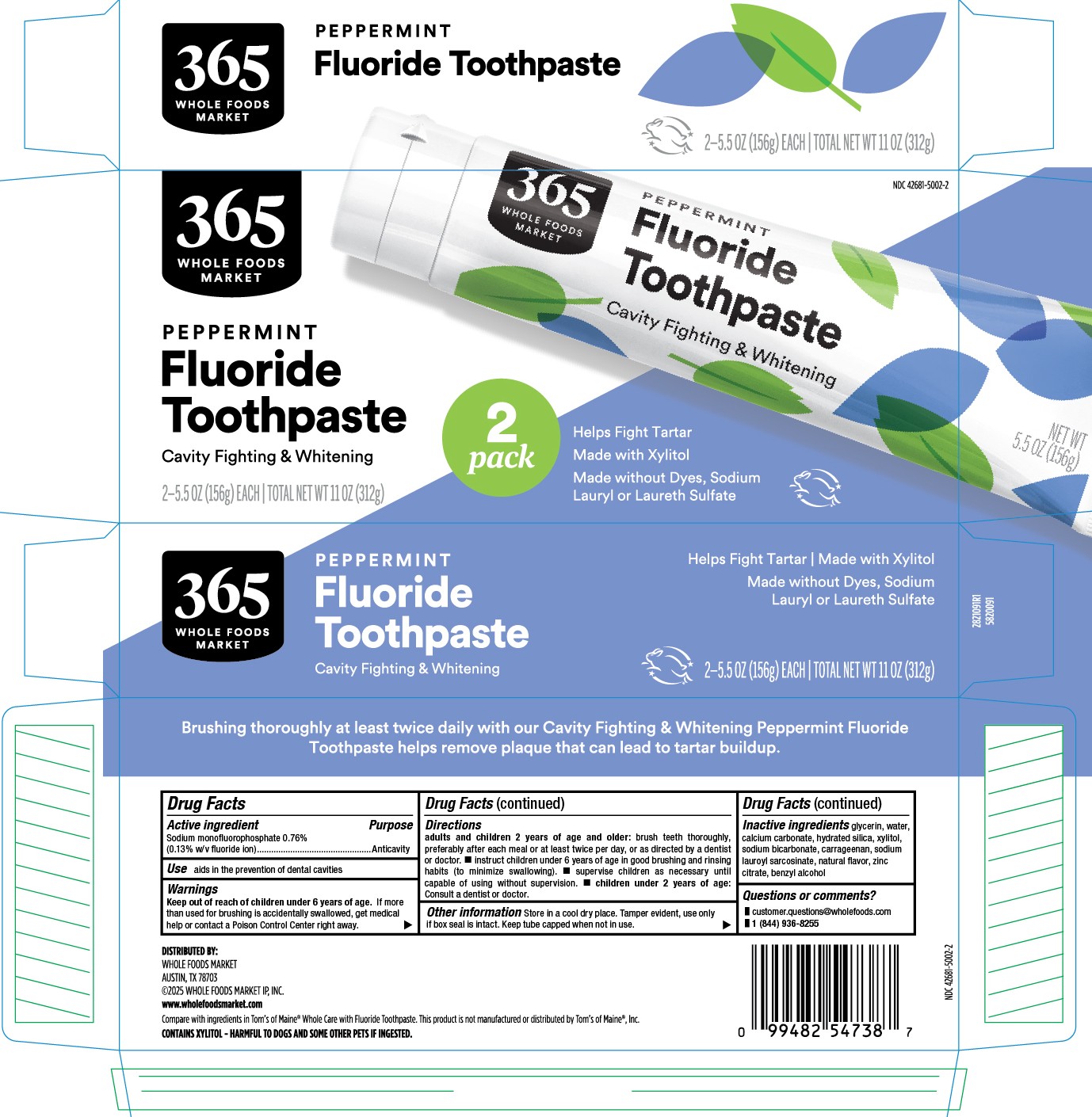 DRUG LABEL: 365 Everyday Value
NDC: 42681-5002 | Form: PASTE, DENTIFRICE
Manufacturer: Whole Foods Market, Inc.
Category: otc | Type: HUMAN OTC DRUG LABEL
Date: 20251121

ACTIVE INGREDIENTS: SODIUM MONOFLUOROPHOSPHATE 0.13 g/100 g
INACTIVE INGREDIENTS: BENZYL ALCOHOL; GLYCERIN; CALCIUM CARBONATE; XYLITOL; SODIUM BICARBONATE; CARRAGEENAN; ZINC CITRATE; HYDRATED SILICA; SODIUM LAUROYL SARCOSINATE; WATER

5820091, 5820002 365 Everyday Value Cavity Fighting & Whitening Peppermint

Drug Facts

Active ingredient

Sodium monofluorophosphate 0.76% (0.13% w/v fluoride ion) ...................... anticavity

Purpose

Anticavity

INDICATIONS AND USAGE

Uses aids in the prevention of dental caviites

Warnings

Keep out of reach of children under 6 years of age. If more than used for brushing is accidentally swallowed, get medical help or contact a Poison Control Center right away.

Directions

Adults and children 2 years of age and older: brush teeth thorughly preferably after each meal or at least twice per day, or as directed by a dentist or doctor.

- Instruct children under 6 years of age in good brushing and rinsing habits (to minimize swallowing).
- Supervise children as necessary until capable of using without supervision.
- children under 2 years of age: consult a dentist or doctor.

INACTIVE INGREDIENT

Inactive ingredients glycerin, water, calcium carbonate, hydrated silica, xylitol, sodium bicarbonate, carrageenan, sodium lauroyl sarcosinate, natural flavor, zinc citrate, benzyl alcohol

Questions or comments?

- customer.questions@wholefoods.com
- 1 (844) 936-8255

DISTRIBUTED BY:

WHOLE FOODS MARKET

AUSTIN, TX 78703

www.wholefoodsmarket.com

MADE IN USA FROM DOMESTIC AND IMPORTED INGREDIENTS